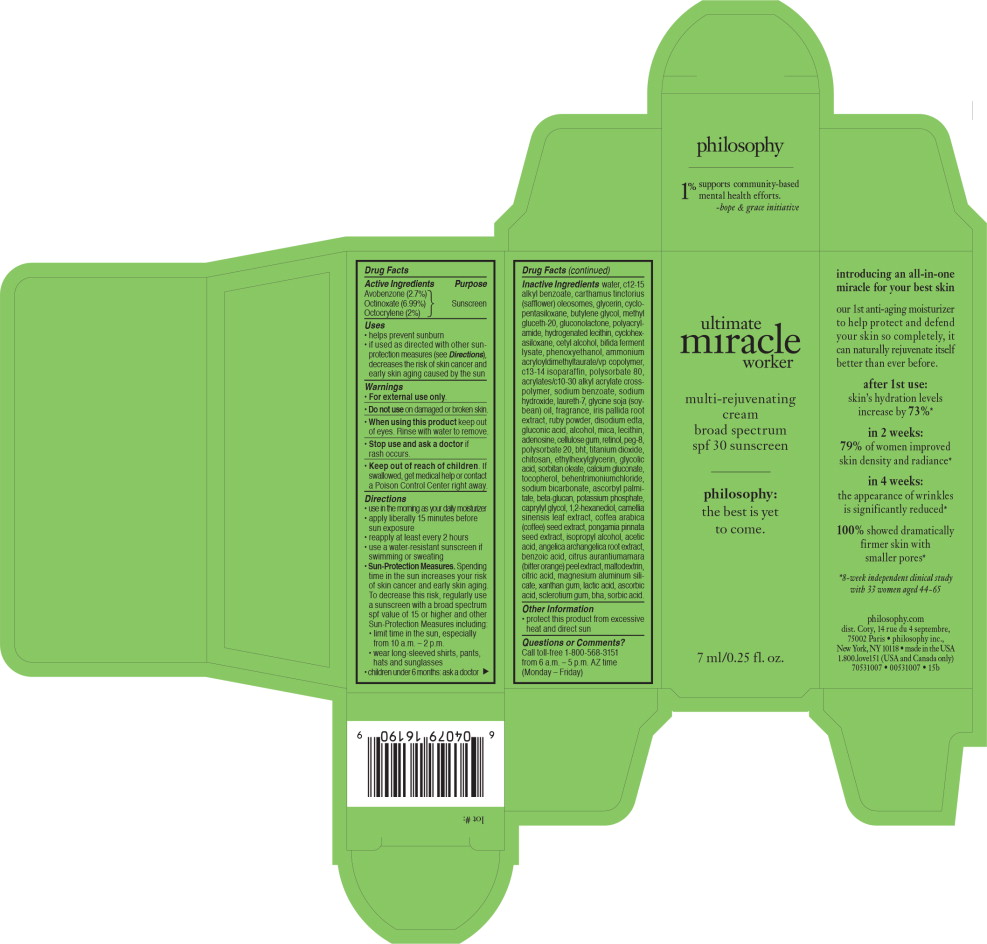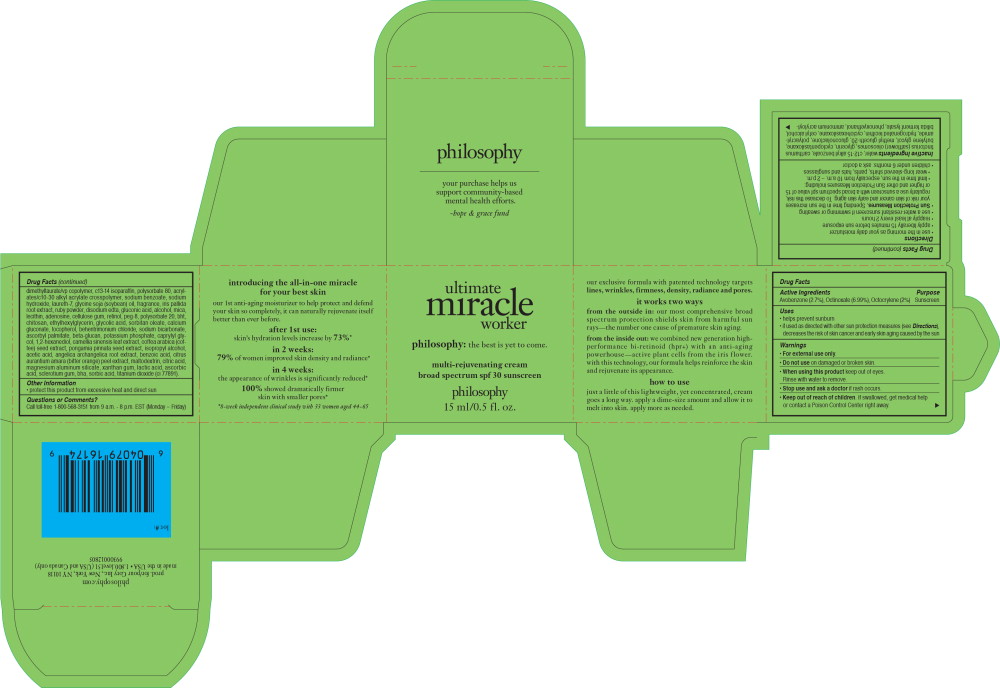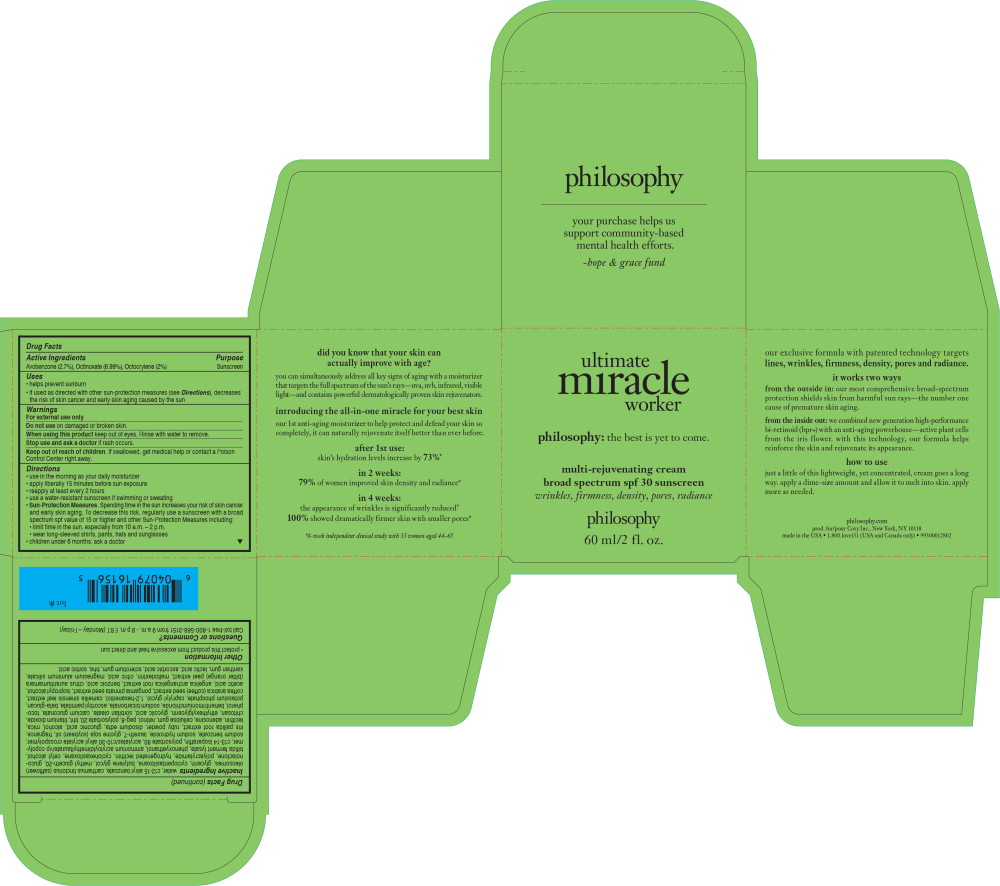 DRUG LABEL: ultimate miracle worker multi-rejuvenating spf 30
NDC: 50184-1013 | Form: CREAM
Manufacturer: Philosophy, Inc.
Category: otc | Type: HUMAN OTC DRUG LABEL
Date: 20241119

ACTIVE INGREDIENTS: OCTOCRYLENE 2 g/100 mL; AVOBENZONE 2.7 g/100 mL; OCTINOXATE 6.99 g/100 mL
INACTIVE INGREDIENTS: WATER; ALKYL (C12-15) BENZOATE; CARTHAMUS TINCTORIUS SEED OLEOSOMES; CALCIUM GLUCONATE; TOCOPHEROL; BEHENTRIMONIUM CHLORIDE; SODIUM BICARBONATE; ASCORBYL PALMITATE; POTASSIUM PHOSPHATE, UNSPECIFIED FORM; CAPRYLYL GLYCOL; CETYL GLYCOL; GREEN TEA LEAF; MILLETTIA PINNATA SEED; ISOPROPYL ALCOHOL; ACETIC ACID; CITRUS AURANTIUM FRUIT RIND; ANGELICA ARCHANGELICA ROOT; BENZOIC ACID; MALTODEXTRIN; CITRIC ACID MONOHYDRATE; MAGNESIUM ALUMINUM SILICATE; XANTHAN GUM; LACTIC ACID, UNSPECIFIED FORM; ASCORBIC ACID; BETASIZOFIRAN; BUTYLATED HYDROXYANISOLE; SORBIC ACID; METHYL GLUCETH-20; GLYCERIN; CYCLOMETHICONE 5; BUTYLENE GLYCOL; GLUCONOLACTONE; POLYACRYLAMIDE (10000 MW); HYDROGENATED SOYBEAN LECITHIN; CYCLOMETHICONE 6; CETYL ALCOHOL; PHENOXYETHANOL; AMMONIUM ACRYLOYLDIMETHYLTAURATE/VP COPOLYMER; C13-14 ISOPARAFFIN; POLYSORBATE 80; SODIUM BENZOATE; SODIUM HYDROXIDE; LAURETH-7; SOYBEAN OIL; IRIS PALLIDA ROOT; EDETATE DISODIUM ANHYDROUS; GLUCONIC ACID; ALCOHOL; MICA; ADENOSINE; CARBOXYMETHYLCELLULOSE SODIUM, UNSPECIFIED FORM; RETINOL; POLYETHYLENE GLYCOL 400; POLYSORBATE 20; BUTYLATED HYDROXYTOLUENE; TITANIUM DIOXIDE; POLIGLUSAM; ETHYLHEXYLGLYCERIN; GLYCOLIC ACID; SORBITAN MONOOLEATE

Ultimate Miracle Worker SPF 30

Drug Facts

Active Ingredients

Avobenzone (2.7%)

Octinoxate (6.99%)

Octocrylene (2%)

Purpose

Sunscreen

Uses

- helps prevent sunburn
- if used as directed with other sun protection measures (see Directions), decreases the risk of skin cancer and early skin aging caused by the sun

Warnings

- For external use only.

- Do not use on damaged or broken skin.

- When using this product keep out of eyes. Rinse with water to remove.

- Stop use and ask a doctor if rash occurs.

- Keep out of reach of children. If swallowed, get medical help or contact a Poison Control Center right away.

Directions

- use in the morning as your daily moisturizer
- apply liberally 15 minutes before sun exposure
- reapply at least every 2 hours
- use a water-resistant sunscreen if swimming or sweating
- Sun-Protection Measures. Spending time in the sun increases your risk of skin cancer and early skin aging. To decrease this risk, regularly use a sunscreen with a broad spectrum spf value of 15 or higher and other Sun-Protection Measures including:
  - limit time in the sun, especially from 10 a.m. – 2 p.m.
  - wear long-sleeved shirts, pants, hats and sunglasses
- children under 6 months: ask a doctor

Inactive Ingredients

water, c12-15 alkyl benzoate, carthamus tinctorius (safflower) oleosomes, glycerin, cyclopentasiloxane, butylene glycol, methyl gluceth-20, gluconolactone, polyacrylamide, hydrogenated lecithin, cyclohexasiloxane, cetyl alcohol, bifida ferment lysate, phenoxyethanol, ammonium acryloyldimethyltaurate/vp copolymer, c13-14 isoparaffin, polysorbate 80, acrylates/c10-30 alkyl acrylate crosspolymer, sodium benzoate, sodium hydroxide, laureth-7, glycine soja (soybean) oil, fragrance, iris pallida root extract, ruby powder, disodium edta, gluconic acid, alcohol, mica, lecithin, adenosine, cellulose gum, retinol, peg-8, polysorbate 20, bht, titanium dioxide, chitosan, ethylhexylglycerin, glycolic acid, sorbitan oleate, calcium gluconate, tocopherol, behentrimoniumchloride, sodium bicarbonate, ascorbyl palmitate, beta-glucan, potassium phosphate, caprylyl glycol, 1,2-hexanediol, camellia sinensis leaf extract, coffea arabica (coffee) seed extract, pongamia pinnata seed extract, isopropyl alcohol, acetic acid, angelica archangelica root extract, benzoic acid, citrus aurantiumamara (bitter orange) peel extract, maltodextrin, citric acid, magnesium aluminum silicate, xanthan gum, lactic acid, ascorbic acid, sclerotium gum, bha, sorbic acid.

Other Information

- protect this product from excessive heat and direct sun

Questions or Comments?

Call toll-free 1-800-568-3151 from 6 a.m. – 5 p.m. AZ time (Monday – Friday)

Principal Display Panel - Ultimate Miracle Worker SPF 30 7 ml Carton Label

ultimate
miracle
worker

multi-rejuvenating
cream
broad spectrum
spf 30 sunscreen

philosophy:
the best is yet
to come.

7 ml/0.25 fl. oz.

Principal Display Panel - Ultimate Miracle Worker SPF 30 15 ml Carton Label

ultimate
miracle
worker

philosophy: the best is yet to come.

multi-rejuvenating cream
broad spectrum spf 30 sunscreen

philosophy

15 ml/0.5 fl. oz.

Principal Display Panel - Ultimate Miracle Worker SPF 30 60 ml Carton Label

ultimate
miracle
worker

philosophy: the best is yet to come.

multi-rejuvenating cream
broad spectrum spf 30 sunscreen

philosophy

60 ml/2 fl. oz.